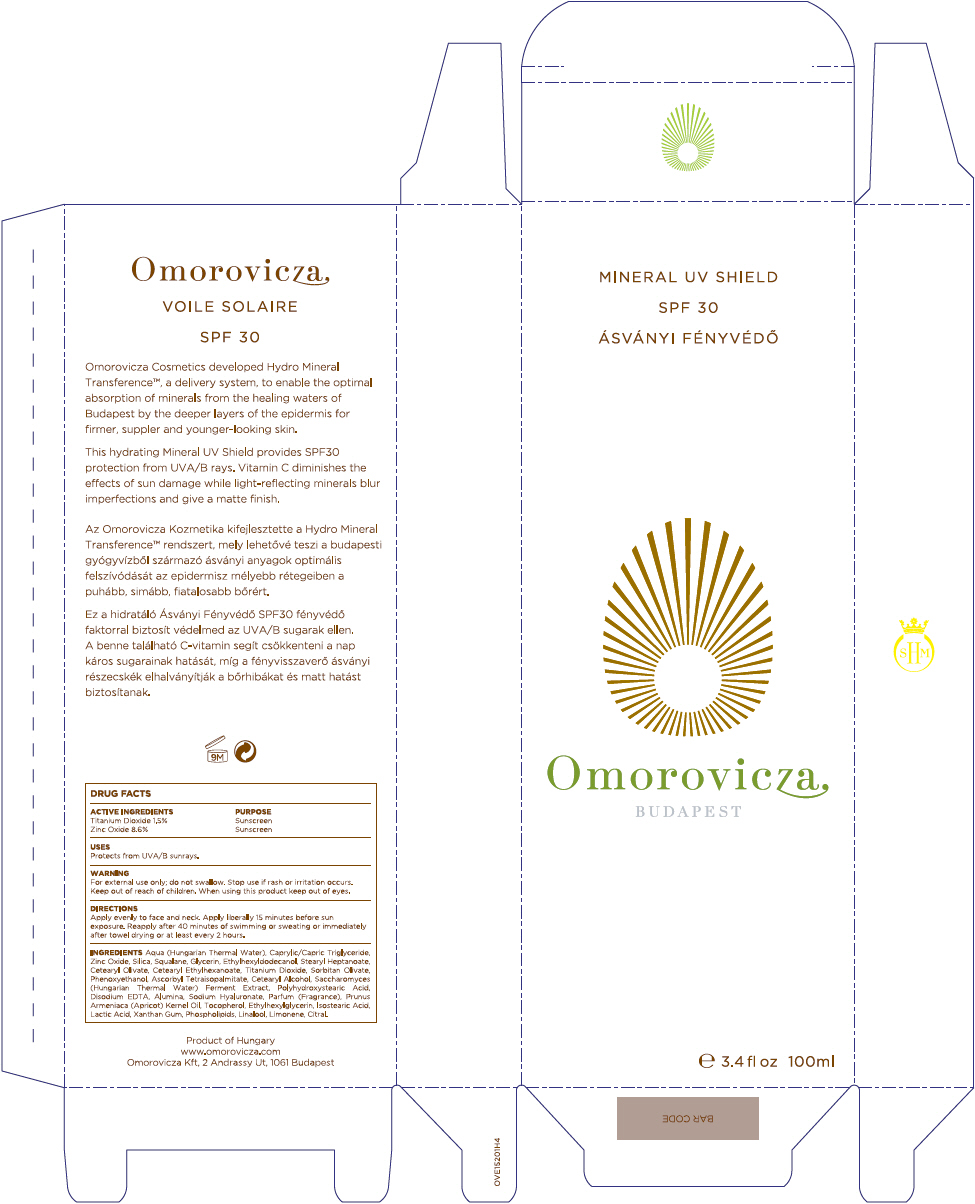 DRUG LABEL: Mineral UV Shield SPF30
NDC: 41442-152 | Form: CREAM
Manufacturer: Omorovicza Kozmetikai Kft.
Category: otc | Type: HUMAN OTC DRUG LABEL
Date: 20140805

ACTIVE INGREDIENTS: Titanium Dioxide 15 mg/1 mL; Zinc Oxide 86 mg/1 mL
INACTIVE INGREDIENTS: Water; Medium-Chain Triglycerides; Silicon Dioxide; Squalane; Glycerin; Stearyl Heptanoate; Cetearyl Olivate; Cetearyl Ethylhexanoate; Sorbitan Olivate; Phenoxyethanol; Ascorbyl Tetraisopalmitate; Cetostearyl Alcohol; Polyhydroxystearic Acid (2300 MW); Edetate Disodium; Aluminum Oxide; Hyaluronate Sodium; Apricot Kernel Oil; Tocopherol; Ethylhexylglycerin; Isostearic Acid; Lactic Acid; Xanthan Gum; Omega-3 Fatty Acids; Linalool, (+/-)-; Citral

Mineral UV Shield SPF30

DRUG FACTS

ACTIVE INGREDIENT

ACTIVE INGREDIENTS | PURPOSE
Titanium Dioxide 1.5% | Sunscreen
Zinc Oxide 8.6% | Sunscreen

USES

Protects from UVA/B sunrays

WARNING

For external use only; do not swallow.

Stop use if rash or irritation occurs.

Keep out of reach for children.

When using this product keep out of eyes.

DIRECTIONS

Apply evenly to face and neck. Apply liberally 15 minutes before sun exposure. Reapply after 40 minutes of swimming or sweating or immediately after towel drying or at least every 2 hours.

INGREDIENTS

Aqua (Hungarian Thermal Water), Caprylic/Capric Triglyceride, Zinc Oxide, Silica, Squalane, Glycerin, Ethylhexyldodecanol, Stearyl Heptanoate, Cetearyl Olivate, Cetearyl Ethylhexanoate, Titanium Dioxide, Sorbitan Olivate, Phenoxyethanol, Ascorbyl Tetraisopalmitate, Cetearyl Alcohol, Saccharomyces (Hungarian Thermal Water) Ferment Extract, Polyhydroxystearic Acid, Disodium EDTA, Alumina, Sodium Hyaluronate, Parfum (Fragrance), Prunus Armeniaca (Apricot) Kernel Oil, Tocopherol, Ethylhexylglycerin, Isostearic Acid, Lactic Acid, Xanthan Gum, Phospholipids, Linalool, Limonene, Citral.

Product of Hungary
www.omorovicza.com
Omorovicza Kft, 2 Andrassy Ut, 1061 Budapest

PRINCIPAL DISPLAY PANEL - 100 ml Tube Box

MINERAL UV SHIELD
SPF 30

Omorovicza
BUDAPEST

e 3.4 fl oz 100ml